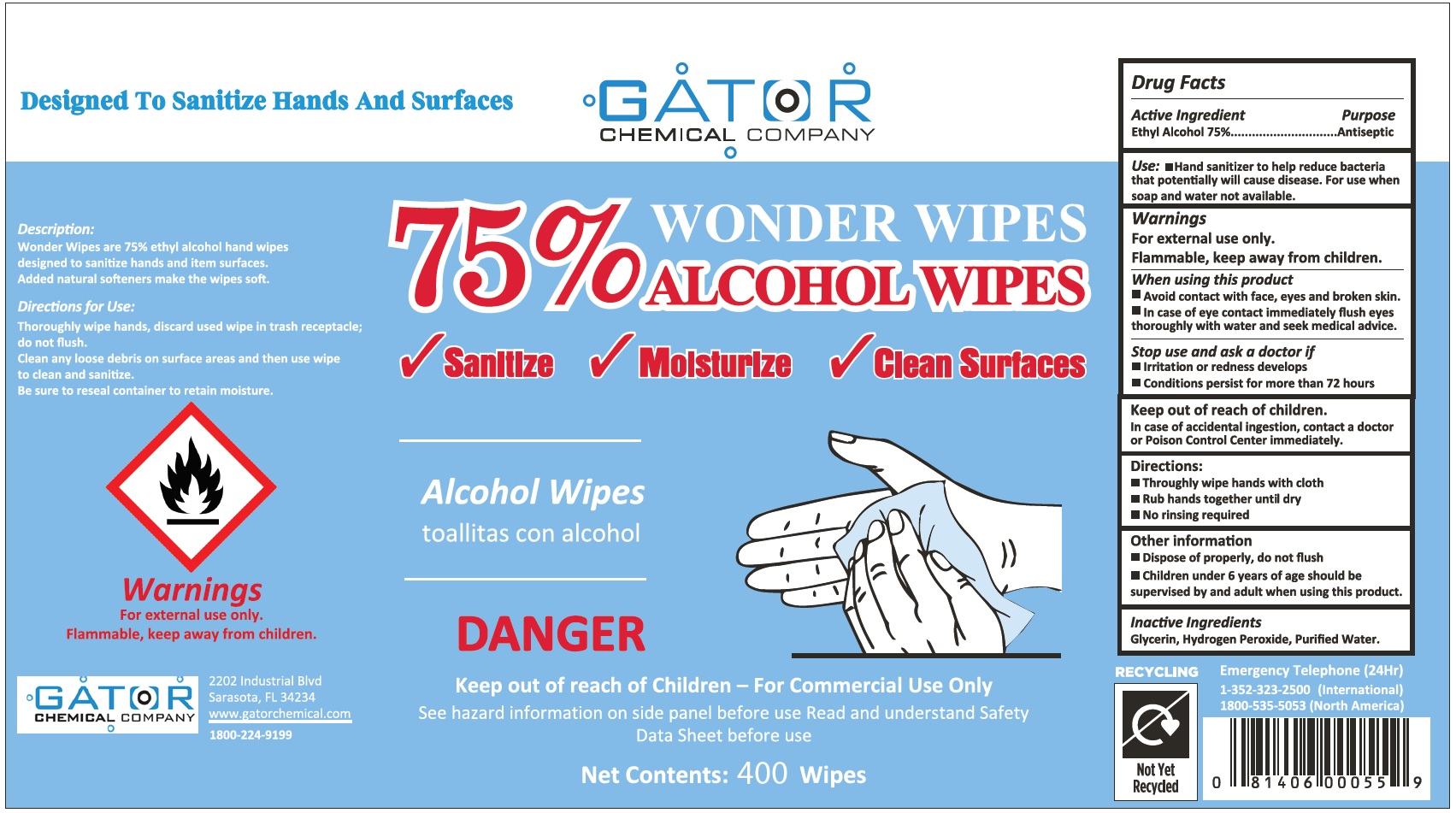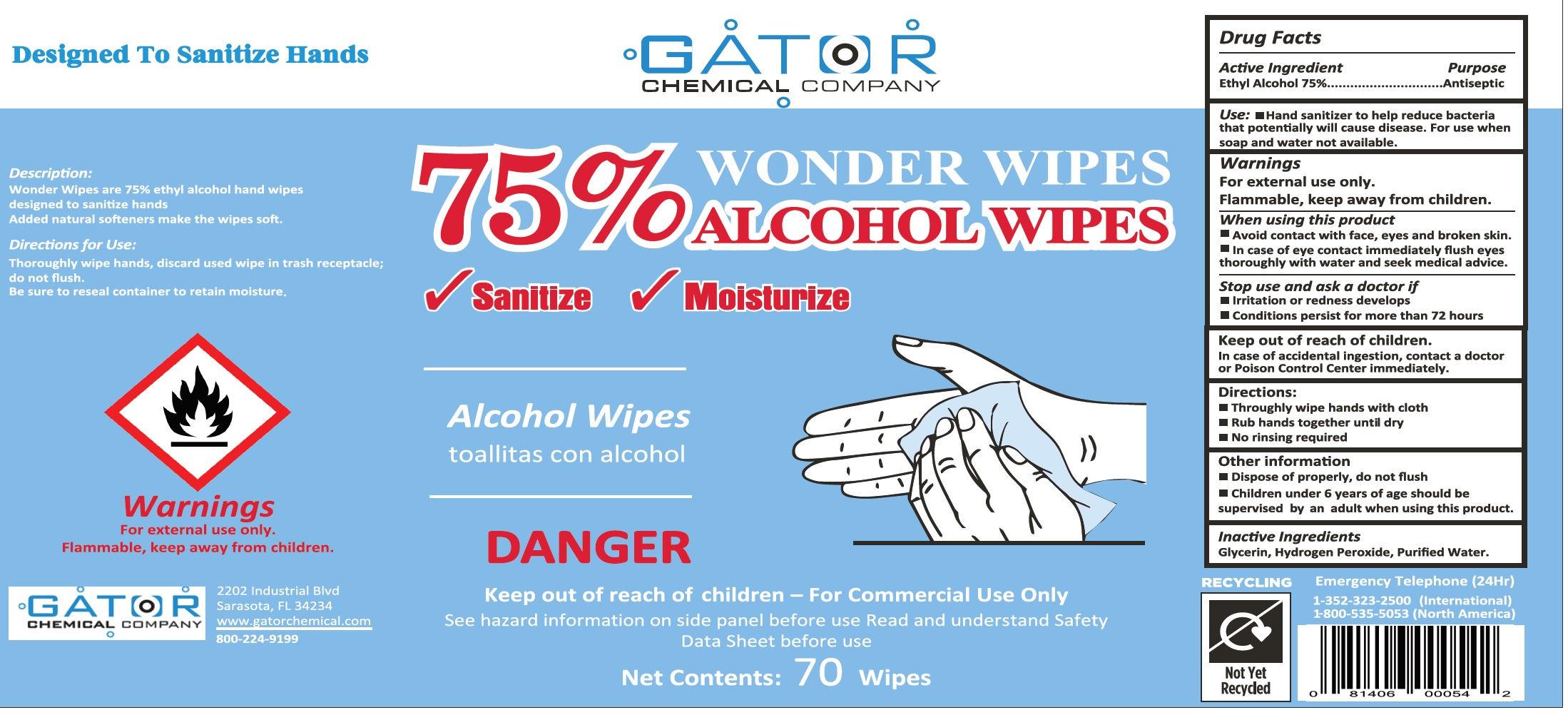 DRUG LABEL: Gator Chemical Company Wonder Wipes
NDC: 77188-003 | Form: CLOTH
Manufacturer: Resource One Inc
Category: otc | Type: HUMAN OTC DRUG LABEL
Date: 20201019

ACTIVE INGREDIENTS: ALCOHOL 0.75 mL/1 mL
INACTIVE INGREDIENTS: GLYCERIN; HYDROGEN PEROXIDE; WATER

Gator Chemical Company Wonder Wipes, 75% Alcohol

Active Ingredient

Ethyl Alcohol 75%

Purpose

Antiseptic

Use:

- Hand sanitizer to help reduce bacteria that potentially will cause disease. For use when soap and water not available.

Warnings

For external use only.

Flammable, keep away from children.

When using this product

- Avoid contact with face, eyes and broken skin.
- In case of eye contact immediately flush eyes thoroughly with water and seek medical advise.

Stop use and ask a doctor if

- Irritation or redness develops
- Conditions persist for more than 72 hours

Keep out of reach of children.

In case of accidental ingestion, contact a doctor or Poison Control Center immediately.

Directions:

- Throughly wipe hands with cloth
- Rub hands together until dry
- No rinsing required

Other information

- Dispose of properly, do not flush
- Children under 6 years of age should be supervised by and adult when using this product.

Inactive Ingredients

Glycerin, Hydrogen Peroxide, Purified Water.